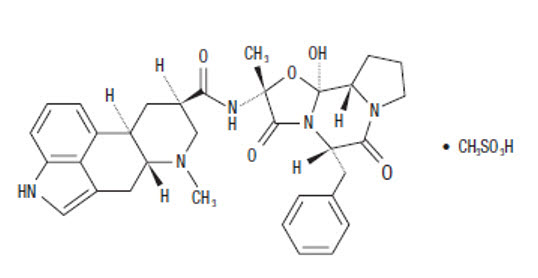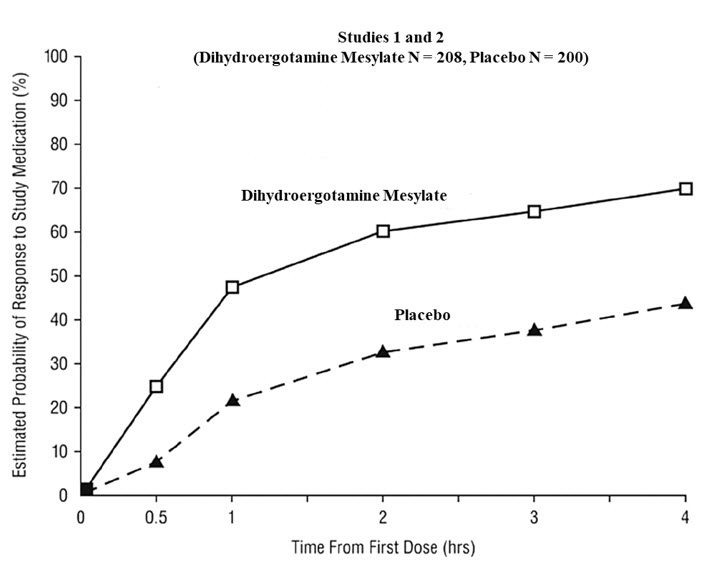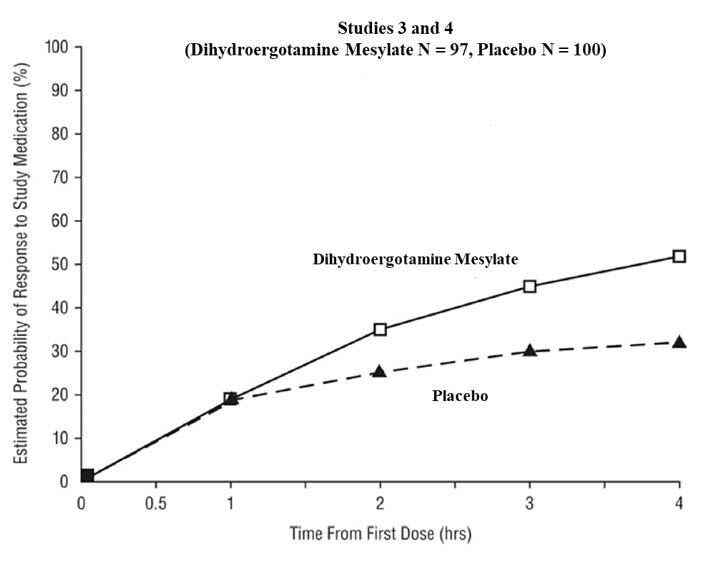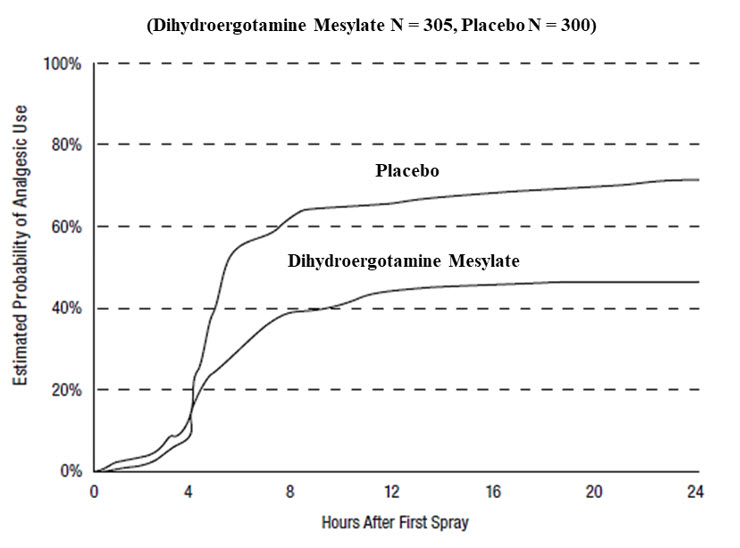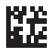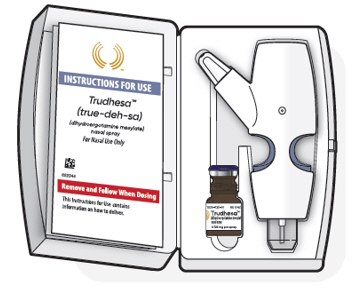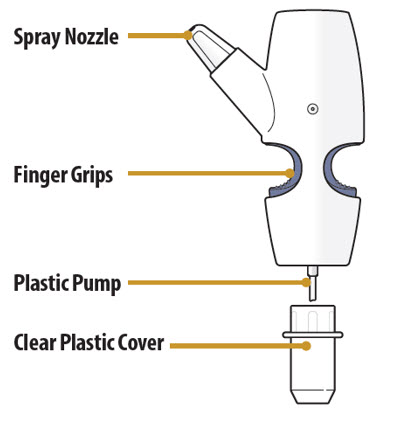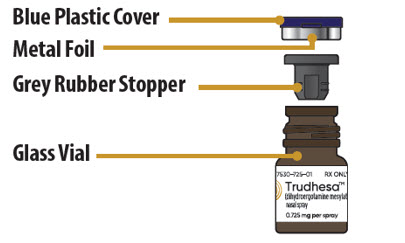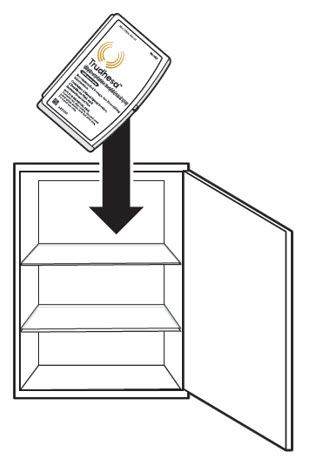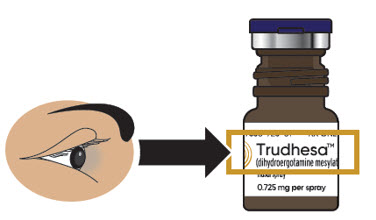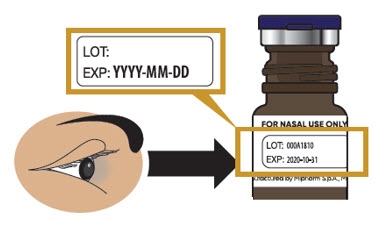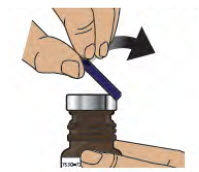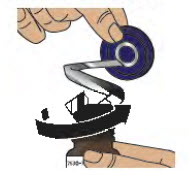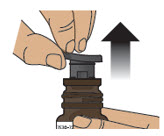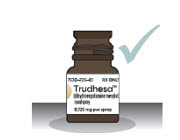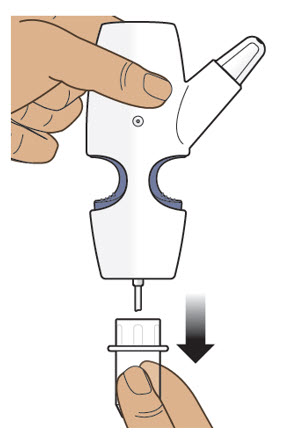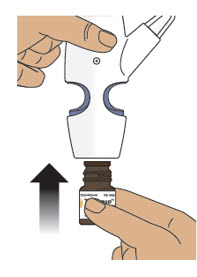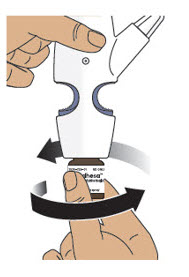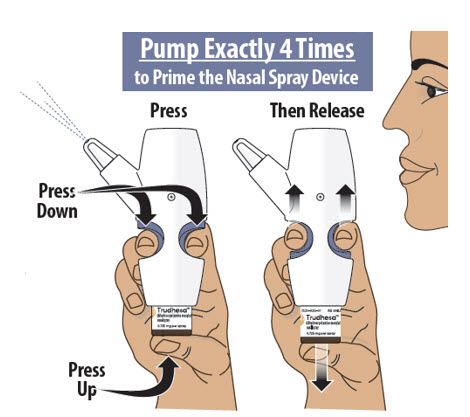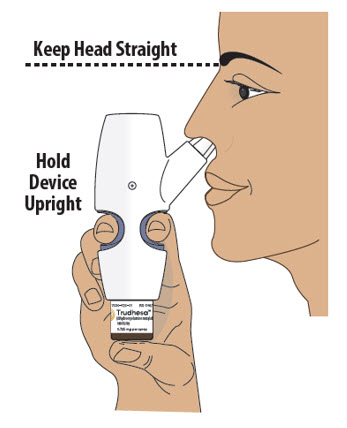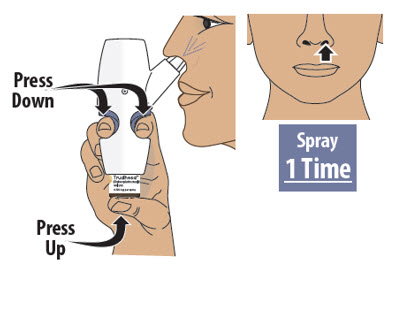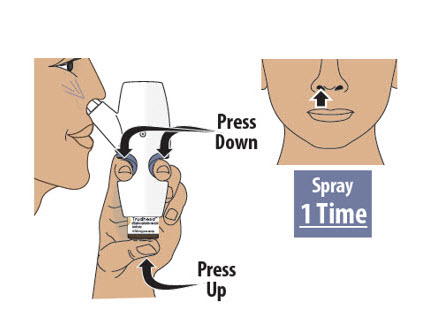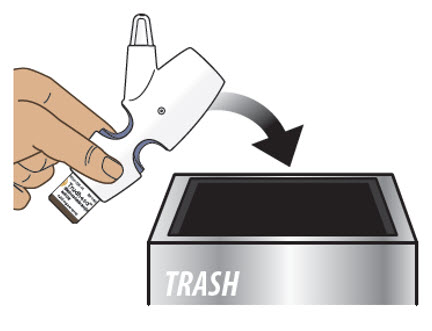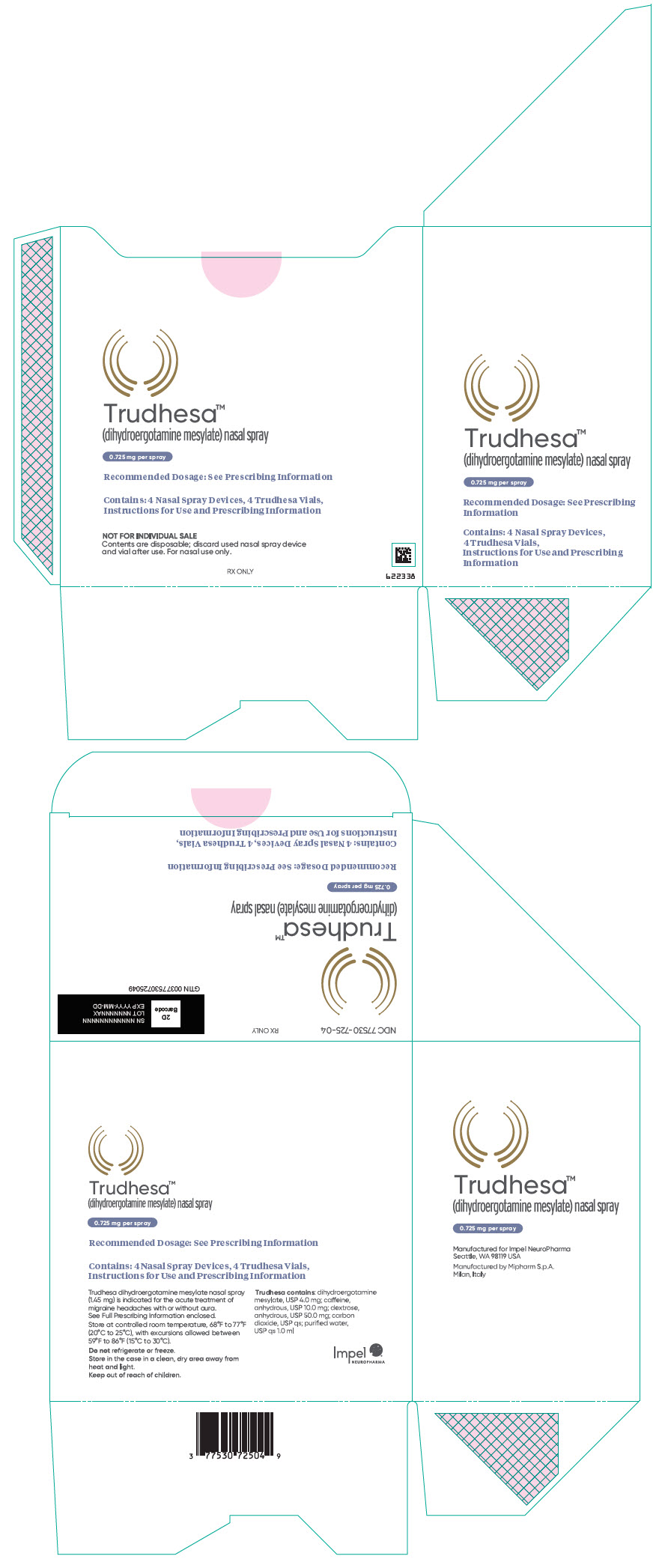 DRUG LABEL: Trudhesa
NDC: 77530-725 | Form: SPRAY, METERED
Manufacturer: Impel Pharmaceuticals LLC
Category: prescription | Type: HUMAN PRESCRIPTION DRUG LABEL
Date: 20250117

ACTIVE INGREDIENTS: Dihydroergotamine mesylate 4 mg/1 mL
INACTIVE INGREDIENTS: Caffeine; Anhydrous Dextrose; Carbon Dioxide; Water

HIGHLIGHTS OF PRESCRIBING INFORMATION

These highlights do not include all the information needed to use TRUDHESA safely and effectively. See full prescribing information for TRUDHESA.
TRUDHESA™ (dihydroergotamine mesylate) nasal spray
Initial U.S. Approval: 1946

WARNING: PERIPHERAL ISCHEMIA FOLLOWING COADMINISTRATION WITH STRONG CYP3A4 INHIBITORS

WARNING: PERIPHERAL ISCHEMIA FOLLOWING COADMINISTRATION WITH POTENT CYP3A4 INHIBITORS

See full prescribing information for complete boxed warning.

Serious and/or life-threatening peripheral ischemia has been associated with the coadministration of dihydroergotamine with strong CYP3A4 inhibitors. Because CYP3A4 inhibition elevates the serum levels of dihydroergotamine, the risk for vasospasm leading to cerebral ischemia and/or ischemia of the extremities is increased. Hence, concomitant use of TRUDHESA with strong CYP3A4 inhibitors is contraindicated. (4, 5.1, 7.1)

1 INDICATIONS AND USAGE

TRUDHESA is an ergotamine derivative indicated for the acute treatment of migraine with or without aura in adults. (1)

Limitations of Use: TRUDHESA is not indicated for the preventive treatment of migraine or for the management of hemiplegic or basilar migraine. (1)

2 DOSAGE AND ADMINISTRATION

- The recommended dose of TRUDHESA is 1.45 mg (administered as one metered spray of 0.725 mg into each nostril). (2.1)
- The dose may be repeated, if needed, a minimum of 1 hour after the first dose. Do not use more than 2 doses within a 24-hour period or 3 doses within 7 days. (2.1)
- Prior to initiation, a cardiovascular evaluation is recommended. (2.2)
- TRUDHESA is for nasal administration only. (2.3)
- Assemble and prime (i.e., pumped 4 times) before use. (2.3)
- Use TRUDHESA immediately after priming and then discard. (2.3)

3 DOSAGE FORMS AND STRENGTHS

Nasal spray: 0.725 mg dihydroergotamine mesylate per spray. (3)

4 CONTRAINDICATIONS

- Concomitant use of strong CYP3A4 inhibitors (4)
- Patients with ischemic heart disease or coronary artery vasospasm (4)
- Patients with uncontrolled hypertension, peripheral arterial diseases, sepsis, following vascular surgery, or severe hepatic or renal impairment (4)
- Patients with hypersensitivity to ergot alkaloids (4)
- Concomitant use of other 5-HT1 agonists (e.g., sumatriptan) or ergotamine-containing or ergot-type medications within 24 hours (4)
- Concomitant use of peripheral and central vasoconstrictors (4)

5 WARNINGS AND PRECAUTIONS

- Myocardial Ischemia and/or Infarction, Other Cardiac Adverse Reactions, and Fatalities: In patients with risk factors, consider 1st dose administration under medical supervision with electrocardiogram. (2.2, 5.2)
- Cerebrovascular Adverse Reactions and Fatalities: Cerebral hemorrhage, subarachnoid hemorrhage and stroke have been reported; discontinue TRUDHESA if suspected. (5.3)
- Other Vasospasm Related Adverse Reactions: TRUDHESA may cause vasospasm or elevation in blood pressure. Discontinue if signs or symptoms of vasoconstriction develop. (5.4, 5.5)
- Medication Overuse Headache: Detoxification may be necessary. (5.6)
- Preterm Labor: Advise pregnant women of the risk. (5.7, 8.1)
- Fibrotic Complications: Pleural and retroperitoneal fibrosis have been reported following prolonged daily use of dihydroergotamine mesylate. Administration of TRUDHESA should not exceed the dosing guidelines or be used for chronic daily administration. (5.8)
- Local Irritation: If severe local irritation occurs for no other attributable reasons, suspend TRUDHESA until resolution. (5.9)

6 ADVERSE REACTIONS

Most common adverse reactions (greater than 1%) were rhinitis, nausea, altered sense of taste, application site reactions, dizziness, vomiting, somnolence, pharyngitis, and diarrhea. (6.1)

To report SUSPECTED ADVERSE REACTIONS, contact Impel NeuroPharma Inc at 1-833-878-3437 or FDA at 1-800-FDA-1088 or www.fda.gov/medwatch.

7 DRUG INTERACTIONS

Beta Blockers/Nicotine: May potentiate/provoke vasoconstriction (7.3, 7.5)

Selective Serotonin Reuptake Inhibitors: Weakness, hyperreflexia, and incoordination may occur with coadministration. (7.6)

8 USE IN SPECIFIC POPULATIONS

- Pregnancy: Based on animal data, may cause fetal harm (8.1)
- Lactation: Advise not to use during breastfeeding. (8.2)

FULL PRESCRIBING INFORMATION

WARNING: PERIPHERAL ISCHEMIA FOLLOWING COADMINISTRATION WITH STRONG CYP3A4 INHIBITORS

Serious and/or life-threatening peripheral ischemia has been associated with the coadministration of dihydroergotamine with strong CYP3A4 inhibitors. Because CYP3A4 inhibition elevates the serum levels of dihydroergotamine, the risk for vasospasm leading to cerebral ischemia and/or ischemia of the extremities is increased. Hence, concomitant use of TRUDHESA with strong CYP3A4 inhibitors is contraindicated [see Contraindications (4), Warnings and Precautions (5.1), and Drug Interactions (7.1)].

1 INDICATIONS AND USAGE

TRUDHESA is indicated for the acute treatment of migraine with or without aura in adults.

Limitations of Use

TRUDHESA is not indicated for the preventive treatment of migraine.

TRUDHESA is not indicated for the management of hemiplegic or basilar migraine.

2 DOSAGE AND ADMINISTRATION

2.1 Dosing Information

The recommended dose of TRUDHESA is 1.45 mg administered as two metered sprays into the nose (one spray of 0.725 mg into each nostril).

The dose may be repeated, if needed, a minimum of 1 hour after the first dose. Do not use more than 2 doses of TRUDHESA within a 24-hour period or 3 doses within a 7-day period.

2.2 Assessment Prior to First Dose

Prior to initiation of TRUDHESA, a cardiovascular evaluation is recommended [see Warnings and Precautions (5.2)]. For patients with risk factors predictive of coronary artery disease who are determined to have a satisfactory cardiovascular evaluation, it is strongly recommended that administration of the first dose of TRUDHESA take place in the setting of an equipped healthcare facility.

2.3 Important Administration Instructions

TRUDHESA is for nasal administration only and must not be injected.

TRUDHESA must be assembled prior to use (see Instructions for Use). Use or discard TRUDHESA within 8 hours once the vial has been opened or the product has been assembled.

Prime the assembled TRUDHESA before initial use by releasing 4 sprays. Use TRUDHESA immediately after priming. Discard TRUDHESA immediately after use. Open and prepare a new TRUDHESA if an additional dose is needed.

3 DOSAGE FORMS AND STRENGTHS

TRUDHESA (dihydroergotamine mesylate) nasal spray is a single-dose, drug-device combination product containing a vial of dihydroergotamine mesylate with a clear and colorless to faintly yellow solution and an intranasal delivery device. Each spray delivers 0.725 mg of dihydroergotamine mesylate.

4 CONTRAINDICATIONS

TRUDHESA is contraindicated in patients:

- with concomitant use of strong CYP3A4 inhibitors, such as protease inhibitors (e.g., ritonavir, nelfinavir, or indinavir), macrolide antibiotics (e.g., erythromycin or clarithromycin), and antifungals (ketoconazole or itraconazole) [see Warnings and Precautions (5.1) and Drug Interactions (7.1)]
- with ischemic heart disease (angina pectoris, history of myocardial infarction, or documented silent ischemia) or patients who have clinical symptoms or findings consistent with coronary artery vasospasm, including Prinzmetal's variant angina [see Warnings and Precautions (5.4)]
- with uncontrolled hypertension [see Warnings and Precautions (5.5)]
- with peripheral arterial disease
- with sepsis
- following vascular surgery
- with severe hepatic impairment
- with severe renal impairment
- with known hypersensitivity to ergot alkaloids
- with recent use (i.e., within 24 hours) of other 5-HT1 agonists (e.g., sumatriptan) or ergotamine-containing or ergot-type medications [see Drug Interactions (7.2)]
- with concomitant use of peripheral and central vasoconstrictors because the combination may result in additive or synergistic elevation of blood pressure [see Warnings and Precautions (5.5)]

5 WARNINGS AND PRECAUTIONS

5.1 Peripheral Ischemia Following Coadministration with Strong CYP3A4 Inhibitors

Serious and/or life-threatening peripheral ischemia has been associated with the coadministration of dihydroergotamine with strong CYP3A4 inhibitors, including protease inhibitors, macrolide antibiotics, and antifungals. Because CYP3A4 inhibition elevates the serum levels of dihydroergotamine, the risk for vasospasm leading to cerebral ischemia and/or ischemia of the extremities is increased. Hence, concomitant use of TRUDHESA with strong CYP3A4 inhibitors is contraindicated [see Contraindications (4) and Drug Interactions (7.1)].

5.2 Myocardial Ischemia and/or Infarction, Other Cardiac Adverse Reactions, and Fatalities

The potential for adverse cardiac adverse reactions exists with TRUDHESA treatment. Serious adverse cardiac events, including some that have been fatal, have occurred following use of dihydroergotamine mesylate. These events have included acute myocardial infarction, life-threatening disturbances of cardiac rhythm (e.g., ventricular tachycardia and ventricular fibrillation), coronary artery vasospasm, and transient myocardial ischemia.

Prior to initiation of TRUDHESA, a cardiovascular evaluation is recommended to determine if the patient is free of coronary artery and ischemic myocardial disease or other significant underlying cardiovascular disease. If, during the cardiovascular evaluation, the patient's medical history (including risk factors), or electrocardiographic investigation, findings are consistent with coronary artery vasospasm or myocardial ischemia, TRUDHESA should not be administered [see Contraindications (4)].

For patients with risk factors predictive of coronary artery disease (e.g., hypertension, hypercholesterolemia, smoker, obesity, diabetes, strong family history of coronary artery disease, females who are surgically or physiologically postmenopausal, or males who are over 40 years of age) who are determined to have a satisfactory cardiovascular evaluation, it is strongly recommended that administration of the first dose of TRUDHESA take place in the setting of an equipped healthcare facility, unless the patient has previously received dihydroergotamine mesylate. During the interval immediately following the first use of TRUDHESA, an electrocardiogram is recommended in those patients with risk factors because ischemia can occur in the absence of clinical symptoms.

5.3 Cerebrovascular Adverse Reactions and Fatalities

The potential for adverse cerebrovascular adverse reactions exists with TRUDHESA treatment. Cerebral hemorrhage, subarachnoid hemorrhage, stroke, and other cerebrovascular events have been reported in patients treated with dihydroergotamine mesylate; and some have resulted in fatalities. In a number of cases, it appears possible that the cerebrovascular events were primary, the dihydroergotamine mesylate having been administered in the incorrect belief that the symptoms experienced were a consequence of migraine, when they were not. It should be noted that patients with migraine may be at increased risk of certain cerebrovascular events (e.g., stroke, hemorrhage, transient ischemic attack). Discontinue TRUDHESA if a cerebrovascular event is suspected.

5.4 Other Vasospasm Related Adverse Reactions

TRUDHESA, like other ergot alkaloids, may cause vasospastic reactions other than coronary artery vasospasm. Myocardial, peripheral vascular, and colonic ischemia have been reported with dihydroergotamine mesylate.

Dihydroergotamine mesylate associated vasospastic phenomena may also cause muscle pains, numbness, coldness, pallor, and cyanosis of the digits. In patients with compromised circulation, persistent vasospasm may result in gangrene or death. TRUDHESA should be discontinued immediately if signs or symptoms of vasoconstriction develop.

Patients who experience other symptoms or signs suggestive of decreased arterial flow, such as ischemic bowel syndrome or Raynaud's syndrome, following the use of any 5-HT agonist, including TRUDHESA, should be evaluated by a healthcare provider.

5.5 Increase in Blood Pressure

Significant elevation in blood pressure has been reported on rare occasions in patients with and without a history of hypertension treated with dihydroergotamine mesylate. TRUDHESA is contraindicated in patients with uncontrolled hypertension [see Contraindications (4)].

An 18% increase in mean pulmonary artery pressure was seen following dosing with another 5-HT1 agonist in a study evaluating subjects undergoing cardiac catheterization.

5.6 Medication Overuse Headache

Overuse of acute migraine drugs (e.g., ergotamines, triptans, opioids, or a combination of these drugs for 10 or more days per month) may lead to exacerbation of headache (i.e., medication overuse headache). Medication overuse headache may present as migraine-like daily headaches or as a marked increase in frequency of migraine attacks. Detoxification of patients including withdrawal of the overused drugs and treatment of withdrawal symptoms (which often includes a transient worsening of headache) may be necessary.

5.7 Preterm Labor

Based on the mechanism of action of dihydroergotamine and findings from the published literature, TRUDHESA may cause preterm labor. Avoid use of TRUDHESA during pregnancy [see Use in Specific Populations (8.1)].

5.8 Fibrotic Complications

The potential for fibrotic complications exists with TRUDHESA treatment. There have been reports of pleural and retroperitoneal fibrosis in patients following prolonged daily use of dihydroergotamine mesylate. Rarely, prolonged daily use of other ergot alkaloid drugs has been associated with cardiac valvular fibrosis. Rare cases have also been reported in association with the use of dihydroergotamine mesylate; however, in those cases, patients also received drugs known to be associated with cardiac valvular fibrosis.

Administration of TRUDHESA should not exceed the dosing guidelines and should not be used for chronic daily administration [see Dosage and Administration (2.1)].

5.9 Local Irritation

Local irritative symptoms were reported in 52% of patients treated with at least one dose of TRUDHESA in an open-labeled trial, which allowed repeated use of TRUDHESA over 6 to 12 months. The most common local irritative symptoms (at least 1% of patients) were nasopharyngitis (21%), rhinitis (19%), nasal discomfort (7%), product taste abnormal/dysgeusia (6%), sinusitis (5%), sinus discomfort (4%), olfactory test abnormal [defined based on a change in score at a prespecified threshold on the University of Pennsylvania Smell Identification Test (UPSIT)] (4%), epistaxis (3%), pharyngitis (3%), nasal mucosal disorder (2%), change in smell (1%), ear discomfort (1%), and rhinorrhea (1%). If a severe local irritation event occurs for no other attributable reasons, TRUDHESA should be temporarily suspended until the event resolves. If the event does not resolve, or it recurs with re-challenge, TRUDHESA should be discontinued permanently. Administration of TRUDHESA should not exceed the dosing guidelines and should not be used for chronic daily administration [see Dosage and Administration (2.1)].

Nasal tissue in animals treated with dihydroergotamine mesylate daily showed mild mucosal irritation characterized by mucous cell and transitional cell hyperplasia and squamous cell metaplasia. Changes in rat nasal mucosa at 64 weeks were less severe than at 13 weeks. Local effects on respiratory tissue after chronic intranasal dosing in animals have not been evaluated.

6 ADVERSE REACTIONS

The following clinically significant adverse reactions are described elsewhere in the labeling:

- Peripheral Ischemia Following Coadministration with Strong CYP3A4 Inhibitors [see Boxed Warning and Warnings and Precautions (5.1)]
- Myocardial Ischemia and/or Infarction, Other Adverse Cardiac Events, and Fatalities [see Warnings and Precautions (5.2)]
- Cerebrovascular Adverse Reactions and Fatalities [see Warnings and Precautions (5.3)]
- Other Vasospasm Related Adverse Reactions [see Warnings and Precautions (5.4)]
- Increase in Blood Pressure [see Warnings and Precautions (5.5)]
- Medication Overuse Headache [see Warnings and Precautions (5.6)]
- Preterm Labor [see Warnings and Precautions (5.7)]
- Fibrotic Complications [see Warnings and Precautions (5.8)]
- Local Irritation [see Warnings and Precautions (5.9)]

6.1 Clinical Trials Experience

Because clinical trials are conducted under widely varying conditions, adverse reaction rates observed in the clinical trials of a drug cannot be directly compared to rates in the clinical trials of another drug and may not reflect the rates observed in practice.

Adverse Reactions in Placebo-Controlled Trials with Dihydroergotamine (DHE) Mesylate Nasal Spray [see Clinical Studies (14)]

Of the 1,796 patients and subjects treated with DHE nasal spray doses 2 mg or less in U.S. and foreign clinical studies, 26 (1.4%) discontinued because of adverse events. The adverse events associated with discontinuation were, in decreasing order of frequency: rhinitis (13), dizziness (2), facial edema (2), and one patient each due to cold sweats, accidental trauma, depression, elective surgery, somnolence, allergy, vomiting, hypotension, and paraesthesia.

Table 1 summarizes the incidence rates of adverse reactions reported by at least 1% of patients who received DHE nasal spray for the treatment of migraine during placebo-controlled, double-blind clinical studies and were more frequent than in those patients receiving placebo. The most commonly reported adverse reactions (greater than 1% of patients who received DHE nasal spray) were rhinitis, nausea, altered sense of taste, application site reactions, dizziness, vomiting, somnolence, pharyngitis, and diarrhea. In most instances these events were transient and self-limited and did not result in patient discontinuation from a study.

Table 1 Adverse Reactions Reported by at Least 1% of the DHE Nasal Spray Treated Patients and Occurred more Frequently than in the Placebo-Group in the Migraine Placebo-Controlled Trials
 | DHE Nasal Spray N=597 % | Placebo N=631 %
Respiratory System
Rhinitis | 26 | 7
Pharyngitis | 3 | 1
Gastrointestinal System
Nausea | 10 | 4
Vomiting | 4 | 1
Diarrhea | 2 | <1
Special Senses, Other
Altered Sense of Taste | 8 | 1
Application Site
Application Site Reaction | 6 | 2
Central and Peripheral Nervous System
Dizziness | 4 | 2
Somnolence | 3 | 2
Body as a Whole, General
Hot Flashes | 1 | <1
Asthenia | 1 | 0
Musculoskeletal System
Stiffness | 1 | <1

Adverse Reactions in Studies with TRUDHESA

An open-label study in adults (18 to 66 years of age) was conducted to evaluate the safety and tolerability of TRUDHESA, repeated use of TRUDHESA was allowed over the course of 6 to 12 months. A total of 354 patients with migraine received at least one dose of TRUDHESA. One hundred and eighty-five patients treated on average at least two migraines per month for 6 months, and 55 patients treated on average at least two migraines per month for 12 months. Of the patients who received at least one dose of TRUDHESA, 185 (52.3%) patients experienced local irritative symptoms. Of these, the most common local irritative symptoms were nasopharyngitis, rhinitis, nasal discomfort, product taste abnormal/dysgeusia, sinusitis, sinus discomfort, olfactory test abnormal, epistaxis, pharyngitis, nasal mucosal disorder, change in smell, ear discomfort, and rhinorrhea [see Warnings and Precautions (5.9)].

6.2 Postmarketing Experience

The following adverse reactions have been identified during postapproval use of dihydroergotamine mesylate. Because these reactions are reported voluntarily from a population of uncertain size, it is not always possible to reliably estimate their frequency or establish a causal relationship to drug exposure:

Vasospasm, paresthesia, hypertension, dizziness, anxiety, dyspnea, headache, flushing, diarrhea, rash, increased sweating, and pleural and retroperitoneal fibrosis after long-term use of dihydroergotamine. Cases of myocardial infarction and stroke have been reported following the use of dihydroergotamine mesylate [see Warnings and Precautions (5.2)].

7 DRUG INTERACTIONS

7.1 CYP3A4 Inhibitors

There have been rare reports of serious adverse events in connection with the coadministration of intravenous administration of dihydroergotamine and strong CYP3A4 inhibitors, such as protease inhibitors (e.g., ritonavir, nelfinavir, indinavir), macrolide antibiotics (e.g., erythromycin, clarithromycin), and antifungals (e.g., ketoconazole, itraconazole), resulting in vasospasm that led to cerebral ischemia and/or ischemia of the extremities [see Warnings and Precautions (5.1)]. The use of strong CYP3A4 inhibitors with dihydroergotamine is contraindicated [see Contraindications (4)]. Administer moderate CYP3A4 inhibitors (e.g., saquinavir, nefazodone, fluconazole, grapefruit juice, fluoxetine, fluvoxamine, zileuton, clotrimazole) with caution.

7.2 Triptans

Triptans (serotonin [5-HT] 1B/1D receptor agonists) have been reported to cause coronary artery vasospasm, and its effect could be additive with TRUDHESA. Therefore, triptans and TRUDHESA should not be taken within 24 hours of each other [see Contraindications (4)].

7.3 Beta Blockers

There have been reports that propranolol may potentiate the vasoconstrictive action of ergotamine by blocking the vasodilating property of epinephrine.

7.4 Vasoconstrictors

TRUDHESA is contraindicated for use with peripheral and central vasoconstrictors because the combination may cause synergistic elevation of blood pressure [see Warnings and Precautions (5.5)].

7.5 Nicotine

Nicotine may provoke vasoconstriction in some patients, predisposing to a greater ischemic response to ergot therapy [see Warnings and Precautions (5.1, 5.5)].

7.6 Selective Serotonin Reuptake Inhibitors

Weakness, hyperreflexia, and incoordination have been reported rarely when 5-HT1 agonists have been coadministered with selective serotonin reuptake inhibitors (e.g., fluoxetine, fluvoxamine, paroxetine, sertraline).

8 USE IN SPECIFIC POPULATIONS

8.1 Pregnancy

Risk Summary

Available data from published literature indicate an increased risk of preterm delivery with TRUDHESA use during pregnancy. Avoid use of TRUDHESA during pregnancy [see Warnings and Precautions (5.7)]. Data collected over decades have shown no increased risk of major birth defects or miscarriage with use of dihydroergotamine mesylate during pregnancy.

In animal studies, adverse effects on embryofetal development were observed following administration of dihydroergotamine mesylate during pregnancy (decreased fetal body weight and/or skeletal ossification) in rats and rabbits or during pregnancy and lactation in rats (decreased body weight and impaired reproductive function in the offspring) in rats at doses less than those used clinically and which were not associated with maternal toxicity (see Data).

The estimated rate of major birth defects (2.2% to 2.9%) and miscarriage (17%) among deliveries to women with migraine are similar to rates reported in women without migraine. All pregnancies have a background risk of birth defect, loss, or other adverse outcomes. In the U.S. general population, the estimated background risk of major birth defects and miscarriages in clinically recognized pregnancies is 2% to 4% and 15% to 20%, respectively.

Data

Animal Data

Intranasal administration of dihydroergotamine mesylate to pregnant rats throughout the period of organogenesis resulted in decreased fetal body weight and/or skeletal ossification at doses of 0.16 mg/day (associated with plasma exposures [AUC] less than that in humans at the maximum recommended human dose [MRHD] of 2.9 mg) or greater. A no-effect level for embryofetal toxicity was not identified in rats. Intranasal administration of dihydroergotamine mesylate to pregnant rabbits throughout organogenesis resulted in decreased skeletal ossification at 3.6 mg/day. At the no-effect dose (1.2 mg/day) for adverse effects on embryofetal development in rabbits, plasma exposures (AUC) were less than that in humans at the MRHD.

Intranasal administration of dihydroergotamine mesylate to female rats throughout pregnancy and lactation resulted in decreased body weight and impaired reproductive function (decreased mating indices) were observed in the offspring at doses of 0.16 mg/day or greater. A no-effect dose for adverse developmental effects in rats was not established.

Effects on development occurred at doses below those that produced evidence of significant maternal toxicity in these studies.

Dihydroergotamine-induced intrauterine growth retardation has been attributed to reduced uteroplacental blood flow resulting from prolonged vasoconstriction of the uterine vessels and/or increased myometrial tone.

8.2 Lactation

Risk Summary

There are no data on the presence of dihydroergotamine in human milk; however, ergotamine, a related drug, is present in human milk. There are reports of diarrhea, vomiting, weak pulse, and unstable blood pressure in breastfed infants exposed to ergotamine. TRUDHESA may reduce milk supply because it may decrease prolactin levels. Because of the potential for reduced milk supply and serious adverse events in the breastfed infant, including diarrhea, vomiting, weak pulse, and unstable blood pressure, advise patients not to breastfeed during treatment with TRUDHESA and for 3 days after the last dose. Breast milk supply during this time should be pumped and discarded.

8.4 Pediatric Use

Safety and effectiveness in pediatric patients have not been established.

8.5 Geriatric Use

Clinical studies of TRUDHESA and other dihydroergotamine mesylate products did not include sufficient numbers of subjects aged 65 and older to determine whether they respond differently from younger subjects. In general, dose selection for an elderly patient should be cautious, usually starting at the low end of the dosing range, reflecting the greater frequency of decreased hepatic, renal, or cardiac function and of concomitant disease or other drug therapy.

9 DRUG ABUSE AND DEPENDENCE

9.1 Controlled Substance

TRUDHESA contains dihydroergotamine (as the mesylate salt), which is not a controlled substance.

9.2 Abuse

Abuse is the intentional, non-therapeutic use of a drug, even once, for its desirable psychological or physiological effects. Currently available data have not demonstrated drug abuse with dihydroergotamine. However, cases of drug abuse in patients on other forms of ergot therapy have been reported.

9.3 Dependence

Physical dependence is a state that develops as a result of physiological adaptation in response to repeated drug use, manifested by withdrawal signs and symptoms after abrupt discontinuation or a significant dose reduction of a drug. Currently available data have not demonstrated physical or psychological dependence with dihydroergotamine. However, cases of psychological dependence in patients on other forms of ergot therapy have been reported.

10 OVERDOSAGE

10.1 Symptoms

Excessive doses of dihydroergotamine may result in peripheral signs and symptoms of ergotism. In general, the symptoms of an acute TRUDHESA overdose are similar to those of an ergotamine overdose, although there may be less pronounced nausea and vomiting with TRUDHESA. The symptoms of an ergotamine overdose include the following: numbness, tingling, pain, and cyanosis of the extremities associated with diminished or absent peripheral pulses; respiratory depression; an increase and/or decrease in blood pressure, usually in that order; confusion, delirium, convulsions, and coma; and/or some degree of nausea, vomiting, and abdominal pain.

In laboratory animals, dihydroergotamine was lethal when given at intravenous doses of 44 mg/kg in mice, 130 mg/kg in rats, and 37 mg/kg in rabbits.

10.2 Treatment

Treatment includes discontinuance of the drug, local application of warmth to the affected area, the administration of vasodilators, and nursing care to prevent tissue damage. Up-to-date information about the treatment of overdosage can often be obtained from a certified Regional Poison Control Center.

11 DESCRIPTION

TRUDHESA (dihydroergotamine mesylate) nasal spray is a single-dose, drug-device combination product containing a dihydroergotamine mesylate drug constituent and a nasal spray device constituent.

The chemical name for dihydroergotamine mesylate is ergotaman-3', 6', 18-trione, 9,10-dihydro-12'-hydroxy-2'-methyl-5'- (phenylmethyl)-, (5'α)-, monomethanesulfonate. Its molecular weight is 679.78, and its molecular formula is C33H37N5O5∙CH4O3S.

The chemical structure is:

Dihydroergotamine mesylate

The drug constituent is a dihydroergotamine mesylate solution. Each milliliter (mL) of solution contains dihydroergotamine mesylate 4.0 mg (equivalent to 3.43 mg dihydroergotamine), and the following inactive ingredients: caffeine (10.0 mg), carbon dioxide (q.s.), dextrose (50.0 mg), and water (q.s. to 1.0 mL).

TRUDHESA nasal spray, after assembly and priming, delivers 0.725 mg dihydroergotamine mesylate per spray. A total dose of 1.45 mg of dihydroergotamine mesylate is delivered in 2 sprays. The nasal spray device contains hydrofluoroalkane-134a (HFA) propellant.

12 CLINICAL PHARMACOLOGY

12.1 Mechanism of Action

Dihydroergotamine binds with high affinity to 5-HT1Dα and 5-HT1Dβ receptors. The therapeutic activity of dihydroergotamine in migraine is generally attributed to the agonist effects at 5-HT1D receptors.

12.2 Pharmacodynamics

Significant elevation in blood pressure has been reported in patients with and without a history of hypertension [see Warnings and Precautions (5.5)].

Dihydroergotamine possesses oxytocic properties [see Warnings and Precautions (5.7)].

12.3 Pharmacokinetics

Absorption

The mean time from dosing to maximum plasma concentration following TRUDHESA administration was approximately 0.5 hours.

Distribution

Dihydroergotamine mesylate is 93% plasma protein bound. The apparent steady-state volume of distribution is approximately 800 liters.

Elimination

Metabolism

Four dihydroergotamine mesylate metabolites have been identified in human plasma following oral administration. The major metabolite, 8'-β-hydroxy dihydroergotamine, exhibits affinity equivalent to its parent for adrenergic and 5-HT receptors and demonstrates equivalent potency in several venoconstrictor activity models, in vivo and in vitro. The other metabolites, i.e., dihydrolysergic acid, dihydrolysergic amide, and a metabolite formed by oxidative opening of the proline ring, are of minor importance. Following nasal administration, total metabolites represent only 20% to 30% of plasma AUC. The systemic clearance of dihydroergotamine mesylate following intravenous and intramuscular administration is 1.5 L/min. Quantitative pharmacokinetic characterization of the four metabolites has not been performed.

Excretion

The major excretory route of dihydroergotamine is via the bile in the feces. The total body clearance is 1.5 L/min, which reflects mainly hepatic clearance. Only 6% to 7% of unchanged dihydroergotamine is excreted in the urine after intramuscular injection. The renal clearance (0.1 L/min) is unaffected by the route of dihydroergotamine administration.

The mean apparent half-life of TRUDHESA nasal administration in healthy subjects is approximately 12 hours.

Specific Populations

No studies have been conducted on the effect of renal or hepatic impairment, gender, race, ethnicity, or pregnancy on dihydroergotamine pharmacokinetics [see Contraindications (4), Use in Specific Populations (8.1)].

Drug Interaction Studies

CYP3A4 Inhibitors

Rare reports of ergotism have been obtained from patients treated with dihydroergotamine and macrolide antibiotics (e.g., clarithromycin, erythromycin) and from patients treated with dihydroergotamine and protease inhibitors (e.g., ritonavir), presumably due to inhibition of CYP3A metabolism of ergotamine [see Contraindications (4)].

Other Drugs

The pharmacokinetics of dihydroergotamine did not appear to be significantly affected by the concomitant use of a local vasoconstrictor.

Multiple oral doses of the β-adrenoceptor antagonist propranolol, used for migraine prophylaxis, had no significant influence on the Cmax, tmax, or AUC of dihydroergotamine doses up to 4 mg. However, propranolol may potentiate the vasoconstrictive action of ergotamine [see Drug Interactions (7.3)].

The effect of oral contraceptives on the pharmacokinetics of TRUDHESA has not been studied.

13 NONCLINICAL TOXICOLOGY

13.1 Carcinogenesis, Mutagenesis, Impairment of Fertility

Carcinogenesis

Assessment of the carcinogenic potential of dihydroergotamine mesylate in mice and rats has not been assessed.

Mutagenesis

Dihydroergotamine mesylate was negative in an in vitro mutagenicity (Ames) assay and positive in in vitro chromosomal aberration (V79 Chinese hamster cell assay with metabolic activation, and human peripheral blood lymphocyte) assays. Dihydroergotamine was negative in in vivo micronucleus assays in mouse and hamster.

Impairment of Fertility

There was no evidence of impairment of fertility in rats given intranasal doses of dihydroergotamine mesylate up to 1.6 mg/day, which was associated with plasma exposures (AUC) approximately 3 times that in humans at the maximum recommended human dose of 2.9 mg/day.

14 CLINICAL STUDIES

The efficacy of TRUDHESA is based on the relative bioavailability of TRUDHESA nasal spray compared to dihydroergotamine mesylate nasal spray in healthy subjects.

The clinical studies described below were conducted using dihydroergotamine mesylate nasal spray.

The efficacy of dihydroergotamine mesylate nasal spray for the acute treatment of migraine headaches was evaluated in four randomized, double-blind, placebo controlled studies in the U.S. The patient population for the trials was predominantly female (87%) and Caucasian (95%) with a mean age of 39 years (range 18 to 65 years). Patients treated a single moderate to severe migraine headache with a single dose of study medication and assessed pain severity over the 24 hours following treatment. Headache response was determined 0.5, 1, 2, 3 and 4 hours after dosing and was defined as a reduction in headache severity to mild or no pain. In studies 1 and 2, a four-point pain intensity scale was utilized; in studies 3 and 4, a five-point scale was used to record pain response. Although rescue medication was allowed in all four studies, patients were instructed not to use them during the four hour observation period. In studies 3 and 4, a total dose of 2 mg was compared to placebo. In studies 1 and 2, doses of 2 and 3 mg were evaluated, and showed no advantage of the higher dose for a single treatment. In all studies, patients received a regimen consisting of 0.5 mg in each nostril, repeated in 15 minutes (and again in another 15 minutes for the 3 mg dose in studies 1 and 2).

The percentage of patients achieving headache response 4 hours after treatment was significantly greater in patients receiving 2 mg doses of dihydroergotamine mesylate nasal spray compared to those receiving placebo in 3 of the 4 studies (see Table 2 and Table 3 and Figure 1 and Figure 2).

Table 2 Studies 1 and 2: Percentage of Patients with Headache Response [Headache response was defined as a reduction in headache severity to mild or no pain. Headache response was based on pain intensity as interpreted by the patient using a four-point pain intensity scale.] 2 and 4 Hours Following a Single Treatment of Study Medication (Dihydroergotamine Mesylate Nasal Spray or Placebo)
 |  | N | 2 hours | 4 hours
Study 1 | Dihydroergotamine mesylate nasal spray | 105 | 61% [p value < 0.001] | 70%
Study 1 | Placebo | 98 | 23% | 28%
 | Difference from Placebo |  | 37% | 42%
Study 2 | Dihydroergotamine mesylate nasal spray | 103 | 47% | 56% [p value < 0.01]
Study 2 | Placebo | 102 | 33% | 35%
 | Difference from Placebo |  | 14% | 21%

Table 3 Studies 3 and 4: Percentage of Patients with Headache Response [Headache response was defined as a reduction in headache severity to mild or no pain. Headache response was evaluated on a five-point scale that included pain response.] 2 and 4 Hours Following a Single Treatment of Study Medication (Dihydroergotamine Mesylate Nasal Spray or Placebo)
 |  | N | 2 hours | 4 hours
Study 3 | Dihydroergotamine mesylate nasal spray | 50 | 32% | 48% [p value < 0.01]
Study 3 | Placebo | 50 | 20% | 22%
 | Difference from Placebo |  | 12% | 26%
Study 4 | Dihydroergotamine mesylate nasal spray | 47 | 30% | 47%
Study 4 | Placebo | 50 | 20% | 30%
 | Difference from Placebo |  | 10% | 17%

The Kaplan-Meier plots below (Figure 1 and Figure 2) provides an estimate of the probability that a patient will have responded to a single 2 mg dose of dihydroergotamine mesylate nasal spray as a function of the time elapsed since initiation of treatment.

Figure 1 Estimated Probability of a Patient Responding During the Four Hours Following a Single 2 mg Dose of Dihydroergotamine Mesylate Nasal Spray as a Function of the Time Elapsed Since Initiation of Treatment [The figure shows the probability over time of obtaining a response following treatment with dihydroergotamine mesylate nasal spray. Headache response was based on pain intensity as interpreted by the patient using a four-point pain intensity scale. Patients not achieving response within 4 hours were censored to 4 hours.]

Figure 2 Estimated Probability of a Patient Responding to Dihydroergotamine Mesylate Nasal Spray During the Four Hours Following Dosing [The figure shows the probability over time of obtaining a response following treatment with dihydroergotamine mesylate nasal spray. Headache response was evaluated on a five-point scale that included pain response. Patients not achieving response within 4 hours were censored to 4 hours.]

For patients with migraine-associated nausea, photophobia, and phonophobia at baseline, there was a lower incidence of these symptoms at 2 and 4 hours following administration of dihydroergotamine mesylate nasal spray compared to placebo.

Patients were not allowed to use additional treatments for 8 hours prior to study medication dosing and during the 4-hour observation period following study treatment. Following the 4-hour observation period, patients were allowed to use additional treatments. For all studies, the estimated probability of patients using additional treatments for their migraines over the 24 hours following the single 2 mg dose of study treatment is summarized in Figure 3 below.

Figure 3 Estimated Probability of a Patient Using Additional Treatments for Migraine Over the 24 Hours Following Either Dihydroergotamine Mesylate Nasal Spray 2 mg (or Placebo) [Kaplan-Meier plot based on data obtained from all studies with patients not using additional treatments censored to 24 hours. All patients received a single treatment of study medication for their migraine attack. The plot also includes patients who had no response to the initial dose.]

Neither age nor sex appear to affect the patient's response to dihydroergotamine mesylate nasal spray. The racial distribution of patients was insufficient to determine the effect of race on the efficacy of dihydroergotamine mesylate nasal spray.

16 HOW SUPPLIED/STORAGE AND HANDLING

16.1 How Supplied

TRUDHESA (dihydroergotamine mesylate) nasal spray (0.725 mg per spray) is supplied as a package of 4 single-dose units (NDC 77530-725-04). Each single-dose unit contains:

- One amber glass vial (NDC 77530-725-01) containing 4 mg dihydroergotamine mesylate in a 1 mL clear and colorless to faintly yellow solution. The stopper is not made with natural rubber latex.
- One nasal spray device.

16.2 Storage and Handling

Store TRUDHESA at controlled room temperature, 20°C to 25°C (68°F to 77°F), with excursions allowed between 15°C to 30°C (59°F to 86°F). Do not refrigerate or freeze.

17 PATIENT COUNSELING INFORMATION

Advise the patient to read the FDA-approved patient labeling (Medication Guide and Instructions for Use).

Serious and/or Life-Threatening Reactions with Coadministration of CYP3A4 Inhibitors

Inform patients that serious and/or life-threatening peripheral ischemia (cerebral ischemia and/or ischemia of the extremities) has been associated with the coadministration of dihydroergotamine mesylate and strong CYP3A4 inhibitors, such as macrolide antibiotics and protease inhibitors [see Contraindications (4), Warnings and Precautions (5.1), and Drug Interactions (7.1)].

Myocardial Ischemia and/or Infarction, Other Cardiac Events, Cerebrovascular Events, and Fatalities

Inform patients of the risk for serious cardiac, cerebrovascular, and other vasospasm related events. Advise patients to notify their healthcare provider if they develop any risk factors or symptoms while taking TRUDHESA. Inform patients that nicotine may provoke vasoconstriction predisposing to a greater ischemic response [see Warnings and Precautions (5.2, 5.3, 5.4)].

Medication Overuse Headache

Inform patients that use of drugs to treat migraine attacks for 10 or more days per month may lead to an exacerbation of headache, and encourage patients to record headache frequency and drug use (e.g., by keeping a headache diary) [see Warnings and Precautions (5.6)].

Local Irritation

Advise patients to notify their healthcare provider if they have bothersome local irritation [see Warnings and Precautions (5.9)].

Drug Interactions

Advise patients to inform their healthcare providers if they are taking, or plan to take, any prescription or over-the-counter drugs, since there is a potential for interactions [see Drug Interactions (7)].

Pregnancy

Advise patients of the risk for preterm birth. Advise women to inform their healthcare provider if they are pregnant or intend to become pregnant [see Warnings and Precautions (5.7), Use in Specific Populations (8.1)].

Lactation

Advise patients not to breastfeed during treatment with TRUDHESA [see Use In Specific Populations (8.2)].

Important Administration Instructions

Advise patients that TRUDHESA must be assembled prior to use and that, prior to administration, the device must be primed (i.e., pumped 4 times). Instruct patients to use or discard TRUDHESA within 8 hours once the vial has been opened or the product has been assembled.

Manufactured by:
Mipharm, S.p.A.
Milano, Italy

Manufactured for:
Impel NeuroPharma Inc
201 Elliott Ave West, Suite 260
Seattle, WA 98119 USA

MEDICATION GUIDE
TRUDHESA™ (true - deh - sa)
(dihydroergotamine mesylate)
nasal spray

What is the most important information I should know about TRUDHESA?
TRUDHESA can cause serious side effects, including:

- Serious problems with blood circulation to your legs and feet (peripheral ischemia). TRUDHESA can cause peripheral ischemia when you take it with certain medicines known as CYP3A4 inhibitors. Peripheral ischemia may lead to a stroke and death. Stop taking TRUDHESA and get emergency medical help right away if you have any of the following symptoms:
  - cramping and pain in your legs or hips
  - feeling of heaviness or tightness in your leg muscles
  - burning or aching pain in your feet or toes while resting
  - numbness, tingling, or weakness in your legs
  - cold feeling or color changes in 1 or both legs or feet
  - slurred speech
  - sudden weakness

Do not take medicines known as strong CYP3A4 inhibitors, such as:

- ritonavir
- nelfinavir

- erythromycin
- clarithromycin

- ketoconazole
- itraconazole

These are not all of the medicines that could affect how TRUDHESA works. Your healthcare provider can tell you if it is safe to take TRUDHESA with other medicines.

What is TRUDHESA?
TRUDHESA is a prescription medicine used for the acute treatment of migraine with or without aura in adults.

- TRUDHESA is not used to prevent migraine.
- TRUDHESA is not used to treat other types of headaches such as hemiplegic (that make you unable to move on one side of your body) or basilar (rare form of migraine with aura) migraines.

It is not known if TRUDHESA is safe and effective in children.

Do not take TRUDHESA if you:

- are taking medicines known as strong CYP3A4 inhibitors.
- have heart problems or a history of heart problems.
- have uncontrolled high blood pressure.
- have narrowing of blood vessels in your legs, arms, stomach, or kidneys (peripheral vascular disease).
- have sepsis.
- have had vascular surgery.
- have severe liver problems.
- have severe kidney problems.
- are allergic to dihydroergotamine mesylate, ergot alkaloids, or any ingredients in TRUDHESA. See the end of this Medication Guide for a complete list of ingredients.
- have taken any of the following medicines in the last 24 hours:
  - sumatriptan
  - almotriptan
  - eletriptan
  - frovatriptan
  - naratriptan
  - rizatriptan
  - ergotamine or ergotamine-type medicines
- have taken any medicines that constrict your blood vessels or raise your blood pressure.

Ask your healthcare provider if you are not sure if you are taking any of these medicines. Your healthcare provider can tell you if it is safe to take TRUDHESA with other medicines.

Before you take TRUDHESA, tell your healthcare provider about all of your medical conditions, including if you:

- have high blood pressure.
- have liver problems.
- have kidney problems.
- smoke.
- are pregnant or plan to become pregnant. TRUDHESA may cause preterm labor. TRUDHESA should be avoided during pregnancy. Talk to your healthcare provider right away if you are pregnant or want to become pregnant.
- are breastfeeding or plan to breastfeed. TRUDHESA may reduce breast milk supply and pass into your breast milk. TRUDHESA may be harmful to your baby. Do not breastfeed your baby while taking TRUDHESA and for 3 days after you use TRUDHESA. Talk with your healthcare provider about the best way to feed your baby if you take TRUDHESA.

Tell your healthcare provider about all the medicines you take, including prescription and over-the-counter medicines, vitamins, and herbal supplements. Your healthcare provider will decide if you can take TRUDHESA with your other medicines.
Especially tell your healthcare provider if you take:

- sumatriptan
- ergot-type medicine
- saquinavir
- nefazodone

- fluconazole
- grapefruit juice
- zileuton
- nicotine

- propranolol or other medicines that can lower your heart rate
- any medicines that can increase your blood pressure
- selective serotonin reuptake inhibitors

These are not all of the medicines that could affect how TRUDHESA works. Your healthcare provider can tell you if it is safe to take TRUDHESA with other medicines.

How should I take TRUDHESA?

- Certain people should take their first dose of TRUDHESA in their doctor's office or in another medical setting. Ask your doctor if you should take your first dose in a medical setting.
- Use TRUDHESA exactly as your healthcare provider tells you to use it. Read and follow the instructions in the Instructions for Use which is provided with the TRUDHESA package before using.
- You should use TRUDHESA as soon as the symptoms of your headache start, but it may be given at any time during a migraine.
- After putting TRUDHESA together and priming the device, spray 1 time in each nostril (a complete dose).
- If your headache comes back after the first complete dose or you only get some relief from your headache, you can use a second dose 1 hour after the first complete dose. Use a new TRUDHESA nasal spray device for the second dose.
- Do not use more than 2 doses of TRUDHESA within a 24-hour period or 3 doses within a 7-day period.
- If you use too much TRUDHESA, call your healthcare provider or go to the nearest hospital emergency room right away.
- Taking TRUDHESA for 10 or more days in 1 month may make your headaches worse. You should write down when you have headaches and when you take TRUDHESA so that you can talk with your healthcare provider about how TRUDHESA is working for you.

What are the possible side effects of TRUDHESA?
TRUDHESA can cause serious side effects, including:
See "What is the most important information I should know about TRUDHESA?"

- Heart attack and other heart problems. Heart problems may lead to death. Stop taking TRUDHESA and get emergency medical help right away if you have any of the following symptoms of a heart attack:
  - discomfort in the center of your chest that lasts for more than a few minutes, or that goes away and comes back
  - severe tightness, pain, pressure, or heaviness in your chest, throat, neck, or jaw
  - pain or discomfort in your arms, back, neck, jaw, or stomach
  - shortness of breath with or without chest discomfort
  - breaking out in a cold sweat
  - nausea or vomiting
  - feeling lightheaded

TRUDHESA is not for people with risk factors for heart disease unless a heart exam is done and shows no problem. You have a higher risk for heart disease if you:

- have high blood pressure
- smoke
- have diabetes

- have high cholesterol levels
- are overweight
- have a family history of heart disease

- Stroke. Stop taking TRUDHESA and get emergency medical help right away if you have any of the following symptoms of a stroke:

- face drooping
- slurred speech

- unusual weakness or numbness

- Changes in color or sensation in your fingers and toes (Raynaud's syndrome).
- Stomach and intestinal problems (gastrointestinal and colonic ischemic events). Symptoms of gastrointestinal and colonic ischemic events include:

- sudden or severe stomach pain
- stomach pain after meals
- weight loss
- nausea or vomiting

- constipation or diarrhea
- bloody diarrhea
- fever

- Increase blood pressure.
- Medicine overuse headache. Some people who use too much TRUDHESA may make their headaches worse (medicine overuse headache). If your headaches get worse, your healthcare provider may decide to stop your treatment with TRUDHESA.
- Preterm labor.
- Tissue changes (fibrotic complications). Inflammation and fiber-like tissue that is not normal (fibrosis) can occur around the lungs and stomach.
- Burning feelings in your nose, mouth and throat and abnormal taste.

The most common side effects of TRUDHESA include:

- runny nose
- nausea
- abnormal taste

- application site reactions
- dizziness
- vomiting

- sleepiness
- sore throat
- diarrhea

These are not all the possible side effects TRUDHESA.
Call your doctor for medical advice about side effects. You may report side effects to FDA at 1-800-FDA-1088.

How should I store TRUDHESA?
Keep TRUDHESA away from heat and light.

- Store TRUDHESA at room temperature between 68°F to 77°F (20°C to 25°C).
- Do not refrigerate or freeze.
- After a TRUDHESA vial has been opened, it must be thrown away after 8 hours.

Keep TRUDHESA and all medicines out of the reach of children.
Do not throw TRUDHESA into fire or incinerators as the canister inside the device may explode.

General information about the safe and effective use of TRUDHESA.
Medicines are sometimes prescribed for purposes other than those listed in a Medication Guide. Do not use TRUDHESA for a condition for which it was not prescribed. Do not give TRUDHESA to other people, even if they have the same symptoms that you have. It may harm them. You can ask your pharmacist or healthcare provider for information about TRUDHESA that is written for health professionals.

What are the ingredients in TRUDHESA?
Active ingredient: Dihydroergotamine mesylate
Inactive ingredients: Caffeine, carbon dioxide, dextrose, and water. The nasal spray device canister contains hydrofluoroalkane-134a (HFA) propellant. The vial stopper is not made with natural rubber latex.
TRUDHESA is a trademark of Impel NeuroPharma Inc.
Marketed by: Impel NeuroPharma, Seattle, WA 98119, USA
www.impelnp.com
Manufactured by: Mipharm, S.p.A. Milano, Italy
Manufactured for: Impel NeuroPharma Inc. 201 Elliott Ave West, Suite 260 Seattle, WA 98119 USA
For more information, go to www.trudhesa.com or call 1-833-878-3437.

This Medication Guide has been approved by the U.S. Food and Drug Administration

Issued: 9/2021

INSTRUCTIONS FOR USE
Trudhesa™
(true-deh-sa)
(dihydroergotamine mesylate)
nasal spray
For Nasal Use Only

622344
Remove and Follow When Dosing
This Instructions for Use contains information on how to deliver Trudhesa.

Introduction
Read this Instructions for Use before you start to use Trudhesa and each time you get a prescription refill. There may be new information.
This information does not take the place of talking with your healthcare provider about your medical condition or treatment. You and your healthcare provider should talk about Trudhesa when you start taking it and at regular checkups.
It is important to follow these directions accurately in order to receive the correct dose. Contact your healthcare provider if you have any questions about how to use this product.

Nasal Spray Device Parts

Glass Vial Parts

Important Information You Need To Know Before Dosing with Trudhesa

- For nasal use only.
- Always prime the nasal spray device before dosing by pumping the finger grips and glass vial together exactly 4 times.
- The purpose of priming is to bring the medicine to the tip of the spray nozzle. You may or may not see liquid or spray come out of the nozzle during each priming action.
- During priming, make sure to aim the spray nozzle away from your face and anything that you do not want coming into contact with the spray of medicine.
- A complete dose is 2 sprays; 1 spray in each nostril.
- Do not take more than 2 doses within a 24-hour period. Do not take more than 3 doses in a 7-day period.
- Always hold the nasal spray device perfectly upright when priming and when dosing.
- Sniffing while dosing is not necessary. However, sniffing will not hurt you nor make the medicine less effective.
- This nasal spray device product is single-dose (for one complete dose only) and should be thrown away (discarded) after use. You will need a new kit for each dose.
- Keep the product in the case until ready to use.
- After a TRUDHESA vial has been opened, it must be thrown away after 8 hours.
- Do not open the glass vial and expose to air until ready to use.
- Store at room temperature in a clean, dry area.
- Do not use if product is damaged.
- Do not use if product is expired.
- Each glass vial and nasal spray device can only be used 1 time. Throw away the entire nasal spray device after dosing, without removing the glass vial.
- You can take another complete dose at least 1 hour after your first dose if your symptoms persist

Storing Trudhesa

- Store Trudhesa at room temperature between 68 °F to 77°F (20 °C to 25°C).
- Store Trudhesa in the original packaging in a clean, dry area away from heat and light (Figure A).
- Keep Trudhesa in the original packaging until you are ready to use.
- Do not refrigerate or freeze Trudhesa.
- Keep Trudhesa and all medicines out of the reach of children.

Figure A

Preparing to Dose with Trudhesa
Step 1: Gather and Check Supplies

1.1 Check to make sure you are using the right medicine for your migraine (see Figure B).
  Figure B
1.2 Check to make sure Trudhesa is not expired (EXP) (see Figure C).
  - If expired, throw away and get a new glass vial.
  Figure C
1.3 Check to make sure that the glass vial and blue plastic cover do not look damaged.

Step 2: Remove Blue Plastic Cover, Metal Foil and Grey Rubber Stopper from Glass Vial

2.1 Remove (flip up) the blue plastic cover from the glass vial (see Figure D).
2.2 Use the blue plastic cover to slowly peel away all the metal foil from the grey rubber stopper in a circular motion (see Figure E).
  NOTE: The metal foil may come off in 2 or more pieces. Make sure to remove all of the metal foil.

Figure D

Figure E

2.3 Pull the grey rubber stopper up and out of the glass vial (Figure F and Figure G).

Figure F

Figure G

2.4 Throw away (discard) cover, foil and grey rubber stopper into the trash.

Step 3: Remove the Clear Plastic Cover from the Nasal Spray Device

3.1 Hold the nasal spray device upright.
3.2 Pull down on the clear plastic cover and remove it from the nasal spray device (Figure H).
  - Throw away the clear plastic cover.
    Figure H

Step 4: Screw the Glass Vial into the Nasal Spray Device

4.1 Hold the nasal spray device upright.
4.2 Gently push glass vial into the bottom of the nasal spray device (see Figure I) and screw it on until it is secured as shown in Figure J.

Figure I

Figure J

Step 5: Prime the Nasal Spray Device by Pumping Four Times with Fin and Thumb

5.1 Hold the nasal spray device upright.
5.2 Point the spray nozzle away from your face.
5.3 Place your thumb on the bottom of the glass vial and place your pointer (index) and middle fingers on the finger grips (see Figure K).
5.4 Pump the nasal spray device exactly 4 times.
  - To pump the nasal spray device, firmly press the finger grips down and press the glass vial up at the same time. Then release (see Figure K).
  - You may see some medicine spray out during priming. This is normal. It is okay if you do not see medicine spray out on the first few pumps.

You may or may not see liquid each time you pump.
Only pump 4 times to prime.
Figure K

Important Tip: The purpose of priming is to bring the medicine to the tip of the spray nozzle. If you do not prime the nasal spray device, you will not get your correct dose of medicine.
Always prime the nasal spray device before use by pumping exactly 4 times.
During priming, make sure to aim the nozzle away from your face and anything that you do not want coming into contact with the spray of medicine.

Using Trudhesa

Step 6: Position the Nasal Spray Device

6.1 Turn or re-grip the nasal spray device so that the spray nozzle faces you.
6.2 Make sure your head is straight and the nasal spray device is upright.
6.3 Insert the spray nozzle into your first nostril as far as comfortable (see Figure L).

Figure L

Step 7: Spray the First Spray into 1 Nostril

Step 8: Spray the Second Spray into Other Nostril

7.1 Firmly press the finger grips down and press the glass vial up at the same time to deliver the first spray (see Figure M). Then release.
  - Only deliver 1 spray into this nostril.
    Figure M

8.1 Move the spray nozzule into your other nostril.
8.2 Firmly press the finger grips down and press the glass vial up at the same time to deliver the second spray (see Figure N). Then release.
  - Only deliver 1 spray into this nostril.
    Figure N

Important Tip: A complete dose is 2 sprays; 1 spray in each nostril.
Do not take more than 2 doses within a 24-hour period. Do not take more than 3 doses in a 7-day period. Please refer to the prescribing information for more information.
Sniffing while or after dosing is not necessary. However, sniffing will not hurt you or make the medicine less effective.

Step 9: Throw away Trudhesa

9.1 Throw away the entire nasal spray device, with the glass vial attached, into your household trash (Figure O).
  Figure O

- Do not separate the glass vial from the nasal spray device.
- Do not reuse the glass vial or the nasal spray device. The glass vial and nasal spray device can only be used 1 time.
- Do not throw Trudhesa into fire or incinerators.

Important Tip: Some medicine may remain in the glass vial. This is normal. Remaining medicine cannot be used for later dosing.

Important Frequently Asked Questions (FAQs)
Question: Can I save medicine by skipping the 4 pumps in "Step 5: Prime the Nasal Spray Device"?
Answer: No. Skipping the 4 pumps to prime the nasal spray device can result in you not getting your correct dose of medicine.
Question: When I first pumped the nasal spray device to prime nothing seemed to happen. Why?
Answer: The purpose of priming is to bring the medicine up to the tip of the nozzle. Even though you may not see or hear anything on your first pump or two, the pumping action will move the medicine from the glass vial through the inside of the nasal spray device and into the nozzle. You should see a spray by your fourth pump attempt. Always prime by pumping exactly 4 times prior to dosing.
Question: Can I reuse the nasal spray device with a new glass vial?
Answer: No. The nasal spray device is for one-time use only and must be thrown away after you have dosed (1 spray in each nostril). This is because the device may clog. After dosing, leave the glass vial screwed onto the nasal spray device and throw away the assembled nasal spray device into the trash. Do not recycle any part of the product.
Question: Can I use the medicine that remains in the glass vial for a later dose?
Answer: No. Although it is normal for some medicine to remain in the glass vial, it can not be used for later dosing. Any leftover medicine will become ineffective.
Question: What happens if I spray more than one time in the same nostril?
Answer: A complete and correct dose is one spray into each nostril. Do not dose in your other nostril if you already sprayed two times in one nostril. Talk to your healthcare provider if you have moderate to severe irritation in your nose or changes in smell.
Question: How soon can I take another dose if I am not getting relief from my migraine?
Answer: You can take another dose at least 1 hour after your first dose if your symptoms persist. Do not take more than 2 doses within a 24-hour period. Do not take more than 3 doses in a 7-day period. Please refer to the prescribing information for more information.

This Instructions for Use has been approved by the U.S. Food and Drug Administration.

Issued: 9/2021

PRINCIPAL DISPLAY PANEL - 0.725 mg Vial Carton

Trudhesa™
(dihydroergotamine mesylate) nasal spray

0.725 mg per spray

Recommended Dosage: See Prescribing Information

Contains: 4 Nasal Spray Devices, 4 Trudhesa Vials,
Instructions for Use and Prescribing Information

NOT FOR INDIVIDUAL SALE
Contents are disposable; discard used nasal spray device
and vial after use. For nasal use only.

RX ONLY

622338